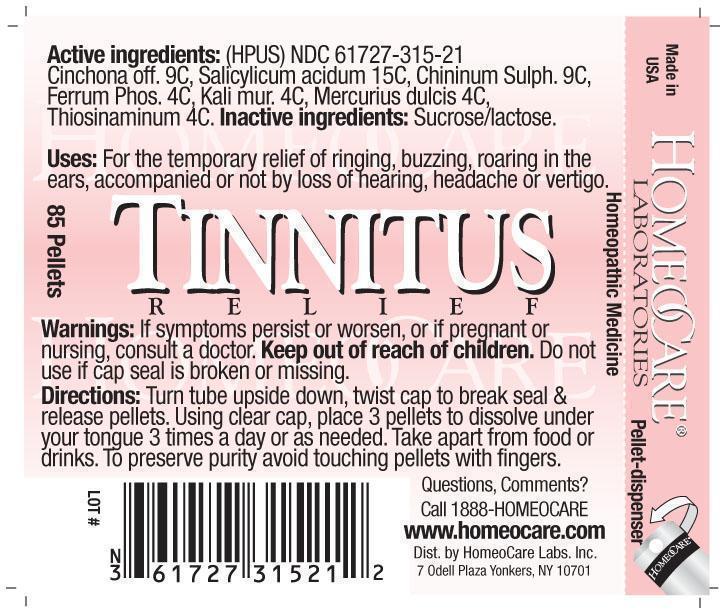 DRUG LABEL: Tinnitus Relief
NDC: 61727-315 | Form: PELLET
Manufacturer: Homeocare Laboratories
Category: homeopathic | Type: HUMAN OTC DRUG LABEL
Date: 20190228

ACTIVE INGREDIENTS: CINCHONA OFFICINALIS BARK 9 [hp_C]/4 g; SALICYLIC ACID 15 [hp_C]/4 g; QUININE SULFATE 9 [hp_C]/4 g; FERRUM PHOSPHORICUM 4 [hp_C]/4 g; POTASSIUM CHLORIDE 4 [hp_C]/4 g; CALOMEL 4 [hp_C]/4 g; ALLYLTHIOUREA 4 [hp_C]/4 g
INACTIVE INGREDIENTS: SUCROSE; LACTOSE

Tinnitus Relief

Active ingredients:

Cinchona off. 9C, Salicylicum acidum 15C, Chininum Sulph. 9C, Ferrum Phos. 4C, Kali mur. 4C, Mercurius dulcis 4C, Thiosinaminum 4C.

Inactive ingredients:

Sucrose/lactose.

Purpose:

For the temporary relief of ringing, buzzing, roaring in the ears, accompanied or not by loss of hearing, headache or vertigo.

Keep out of reach of children.

Indications & Usage:

Turn tube upside down, twist cap to break seal & release pellets. Using clear cap, place 3 pellets to dissolve under your tongue 3 times a day or as needed. Take apart from food or drinks. To preserve purity avoid touching pellets with fingers.

Warnings:

If symptoms persist or worsen, or if pregnant or nursing, consult a doctor. Keep out of reach of children. Do not use if cap seal is broken or missing.

Dosage and Administration:

Turn tube upside down, twist cap to break seal & release pellets. Using clear cap, plce 3 pellets to dissolve under your tongue 3 times a day or as needed. Take apart from food or drinks. To preserve purity avoid touching pellets with fingers.

Tinnitus Relief:

Homeopathic Medicine

85 Pellets

hcl_label_tinnitus 2012.jpg